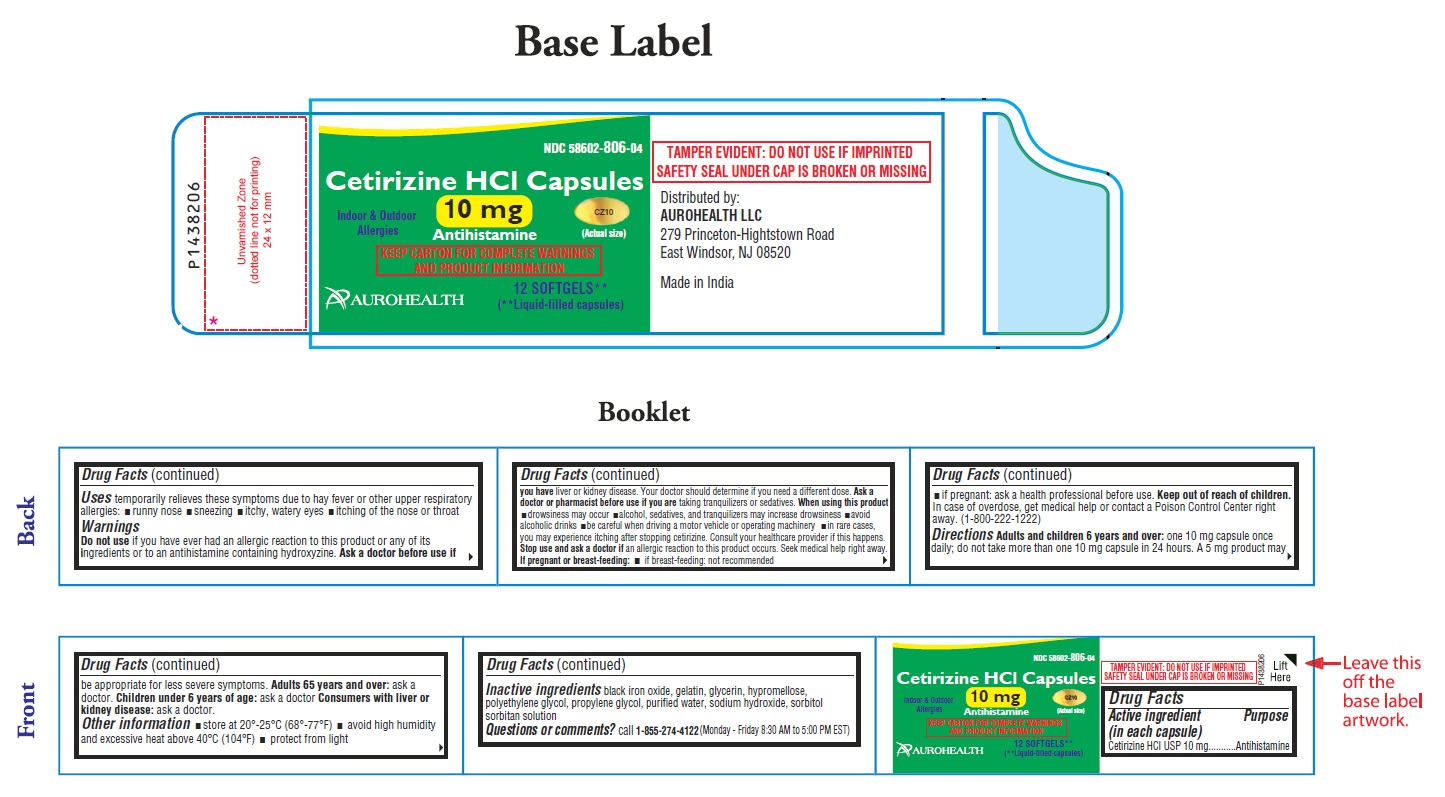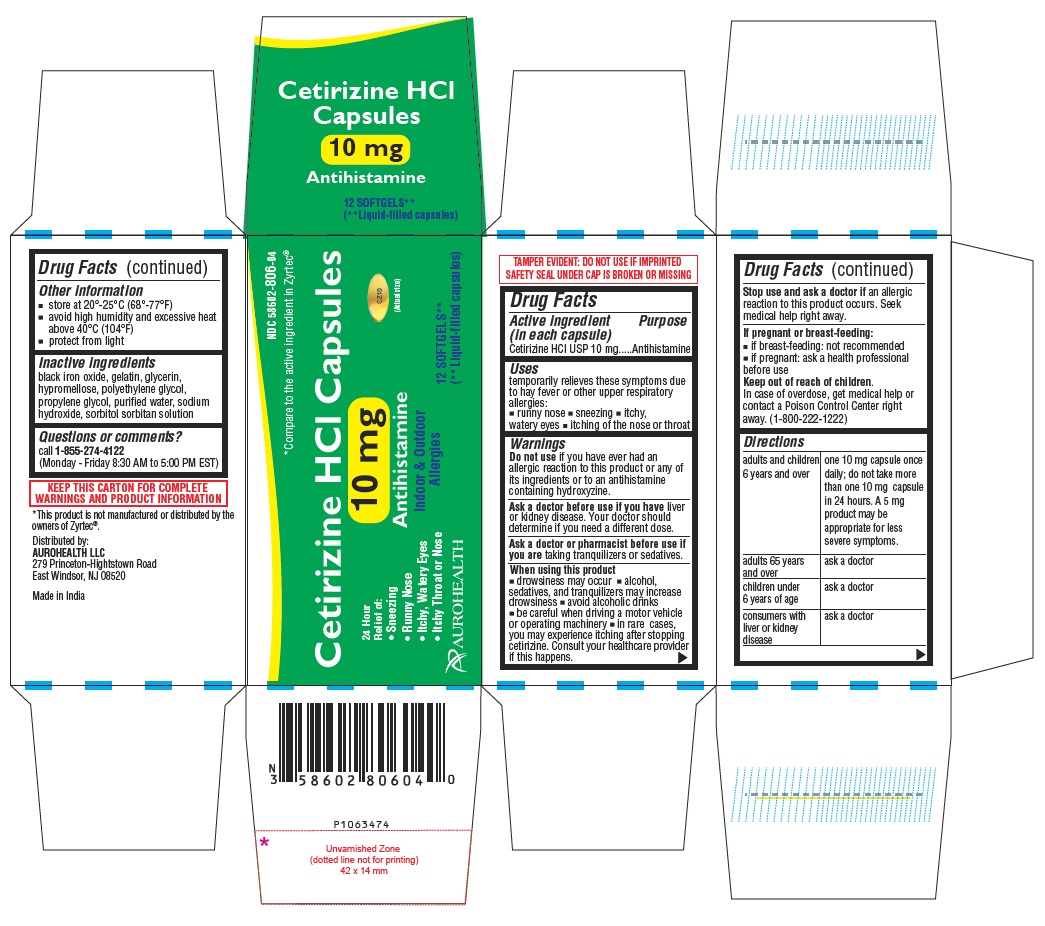 DRUG LABEL: Cetirizine Hydrochloride (Allergy)
NDC: 58602-806 | Form: CAPSULE
Manufacturer: Aurohealth LLC
Category: otc | Type: Human OTC Drug Label
Date: 20260226

ACTIVE INGREDIENTS: CETIRIZINE HYDROCHLORIDE 10 mg/1 1
INACTIVE INGREDIENTS: FERROSOFERRIC OXIDE; GELATIN, UNSPECIFIED; GLYCERIN; HYPROMELLOSE 2910 (6 MPA.S); POLYETHYLENE GLYCOL 400; PROPYLENE GLYCOL; WATER; SODIUM HYDROXIDE; SORBITOL

Cetirizine HCl Capsules 10 mg (Allergy)
Drug Facts

Active ingredient (in each capsule)

Cetirizine HCl USP 10 mg

Purpose

Antihistamine

Uses

temporarily relieves these symptoms due to hay fever or other upper respiratory allergies:

- runny nose
- sneezing
- itchy, watery eyes
- itching of the nose or throat

Warnings

Do not use if you have ever had an allergic reaction to this product or any of its ingredients or to an antihistamine containing hydroxyzine.

Ask a doctor before use if you have liver or kidney disease. Your doctor should determine if you need a different dose.

Ask a doctor or pharmacist before use if you are taking tranquilizers or sedatives.

When using this product

- drowsiness may occur
- alcohol, sedatives, and tranquilizers may increase drowsiness
- avoid alcoholic drinks
- be careful when driving a motor vehicle or operating machinery
- in rare cases, you may experience itching after stopping cetirizine. Consult your healthcare provider if this happens.

Stop use and ask a doctor if

an allergic reaction to this product occurs. Seek medical help right away.

If pregnant or breast-feeding:

- if breast-feeding: not recommended
- if pregnant: ask a health professional before use.

Keep out of reach of children.

In case of overdose, get medical help or contact a Poison Control Center right away. (1-800-222-1222)

Directions

adults and children 6 years and over | one 10 mg capsule once daily; do not take more than one 10 mg capsule in 24 hours. A 5 mg product may be appropriate for less severe symptoms.
adults 65 years and over | ask a doctor
children under 6 years of age | ask a doctor
consumers with liver or kidney disease | ask a doctor

Other information

- store at 20°-25°C (68°-77°F)
- avoid high humidity and excessive heat above 40°C (104°F)
- protect from light

Inactive ingredients

black iron oxide, gelatin, glycerin, hypromellose, polyethylene glycol, propylene glycol, purified water, sodium hydroxide, sorbitol sorbitan solution

Questions or comments?

call 1-855-274-4122 (Monday - Friday 8:30 AM to 5:00 PM EST)

*This product is not manufactured or distributed by the owners of Zyrtec®.
Distributed by:
AUROHEALTH LLC
279 Princeton-Hightstown Road
East Windsor, NJ 08520

Made in India

PACKAGE LABEL-PRINCIPAL DISPLAY PANEL - 10 mg (12's Capsule Container Label)

NDC 58602-806-04
Cetirizine HCl Capsules
10 mg
Antihistamine
Indoor & Outdoor
Allergies
CZ10
(Actual size)

KEEP CARTON FOR COMPLETE WARNINGS
AND PRODUCT INFORMATION

AUROHEALTH
12 SOFTGELS**

(** Liquid-filled capsules)

PACKAGE LABEL-PRINCIPAL DISPLAY PANEL -10 mg (12's Capsule Container Carton Label)

NDC 58602-806-04
*Compare to the active ingredient in Zyrtec®
Cetirizine HCl Capsules
10 mg
Antihistamine
Indoor & Outdoor CZ10
Allergies (Actual size)
24 HOUR
Relief of:

- Sneezing
- Runny Nose
- Itchy, Watery Eyes
- Itchy Throat or Nose

AUROHEALTH

12 SOFTGELS**
(** Liquid-filled capsules)